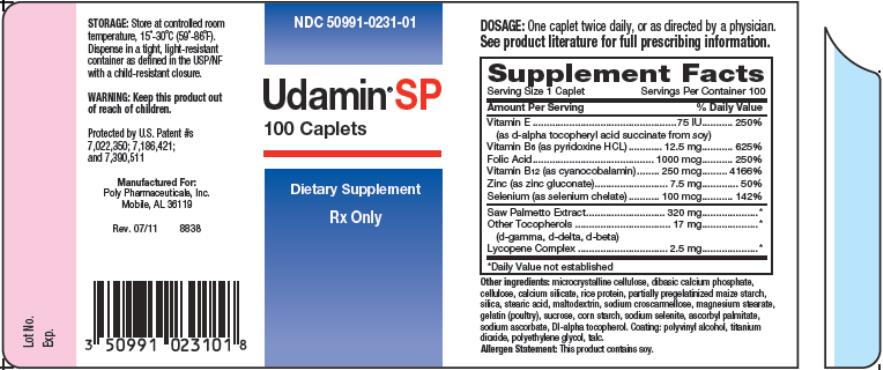 DRUG LABEL: UDAMIN SP
NDC: 50991-231 | Form: CAPSULE, COATED
Manufacturer: Poly Pharmaceuticals, Inc.
Category: other | Type: DIETARY SUPPLEMENT
Date: 20150522

ACTIVE INGREDIENTS: .ALPHA.-TOCOPHEROL 75 [iU]/1 1; PYRIDOXINE 12.5 mg/1 1; FOLIC ACID 1000 ug/1 1; CYANOCOBALAMIN 250 ug/1 1; ZINC 7.5 mg/1 1; SELENIUM 100 ug/1 1; SAW PALMETTO 320 mg/1 1; TOCOPHEROL 17 mg/1 1; LYCOPENE 2.5 mg/1 1
INACTIVE INGREDIENTS: CELLULOSE, MICROCRYSTALLINE; CALCIUM PHOSPHATE, MONOBASIC, ANHYDROUS; POWDERED CELLULOSE; CALCIUM SILICATE; STARCH, CORN; SILICON DIOXIDE; STEARIC ACID; MALTODEXTRIN; CROSCARMELLOSE SODIUM; MAGNESIUM STEARATE; GELATIN; SUCROSE; SODIUM SELENITE; ASCORBYL PALMITATE; SODIUM ASCORBATE; .ALPHA.-TOCOPHEROL, DL-; POLYVINYL ALCOHOL; TITANIUM DIOXIDE; POLYETHYLENE GLYCOLS; TALC

UDAMIN SP Caplets

STATEMENT OF IDENTITY:

UDAMIN SP caplets for oral administration is a 90-day dietary supplement that consists of 100 white film-coated, capsule shaped tablet each debossed with “PE820”.

WARNING:

Folic acid alone is improper therapy in the treatment of pernicious anemia and other megaloblastic anemias where Vitamin B12 is deficient.

SAFE HANDLING WARNING:

Keep this product out of reach of children. In case of accidental overdose, call a doctor or poison control center immediately.

DOSAGE AND ADMINISTRATION:

Adults: One caplet twice daily, or as directed by a physician. UDAMIN SP is not recommended for women or adolescents.

Supplement Facts

Serving Size 1 Caplet Servings Per Container 100

Each White, Film-coated Capsule Shaped Tablet (caplet) for Oral Administration Contains)

Vitamin E

(as d-alpha tocopheryl acid succinate from soy) ..............75 IU

Vitamin B6

(as pyridoxine HCL) ......................................................12.5 mg

Folic Acid ................................................................... 1000 mcg

Vitamin B12

(as cyanocobalamin) ....................................................250 mcg

Zinc

(as zinc gluconate) .........................................................7.5 mg

Selenium

(as selenium chelate) ...................................................100 mcg

Saw Palmetto Extract ...................................................320 mg*

Other tocopherols:

(d-gamma, d-delta, d-beta) ..............................................17 mg

Lycopene Complex ..........................................................2.5 mg

*Yielding 144 mg of active ingredients, including free fatty acids.

OTHER INGREDIENTS: Each caplet also contains the following inactive ingredients: microcrystalline cellulose, dibasic calcium phosphate, cellulose, calcium silicate, rice protein, partially pregelatinized maize starch, silica, stearic acid, maltodextrin, sodium croscarmellose, magnesium stearate, gelatin (poultry), sucrose, corn starch, sodium selenite, ascorbyl palmitate, sodium ascorbate, Dl-alpha tocopherol. Coating: polyvinyl alcohol, titanium dioxide, polyethylene glycol, talc.

HOW SUPPLIED: White film-coated, capsule shaped tablet—supplied in bottles of 100. Debossed with “PE820”. Store at controlled room temperature between 15°-30°C (59°-86°F).

Dispense in a tight, light resistant container as defined in the USP/NF with a child-resistant closure. NDC#50991-0231-01, 100 caplets per bottle. The listed product number is not a National Drug Code. Instead, Poly Pharmaceuticals has assigned a product code formatted according to standard industry practice to meet the formatting requirements of pharmacy and health insurance computer systems.

PRECAUTIONS/WARNING:

Folic acids in doses above 0.1 mg daily may obscure pernicious anemia in that hematologic remission can occur while neurological manifestations remain progressive. The 250 mcg of Vitamin B12 (as cyanocobalamin) contained in each caplet of UDAMIN SP should address this precaution.

Adverse Reactions

Allergic sensitization has been reported following both oral and parental administration of folic acid. Paresthesia, somnolence have been reported with pyridoxine HCl.

Drug Interactions

Pyridoxine daily can decrease the efficacy of levodopa in the treatment of Parkinsonism. However, this vitamin may be used concurrently in patients receiving a preparation containing both carbidopa and levodopa. Concurrent use of phenytoin and folic acid may result in decreased phenytoin effectiveness.

STORAGE: Store controlled room temperature, 15°- 30°C (59°- 86°F)

HEALTH CLAIMS:

Because toxic reactions have been reported with injudicious use of certain vitamins and minerals, patients should be instructed to follow physician’s dosage regimen.

ALLERGEN STATEMENT: This product contains soy.

CONTRAINDICATIONS: UDAMIN SP is contraindicated in patients with a known hypersensitivity to any of its ingredients.

PRINCIPAL DISPLAY PANEL

– 100 Caplets container label

50991-231-01 RX ONLY

Udamin SP

DIETARY SUPPLEMENT

Manufactured For:
Poly Pharmaceuticals, Inc
Mobile, AL 36119

Protected by U.S. Patent #'s 7,002,350;7,186,421; and 7,390,511

Revised 07/11 8838